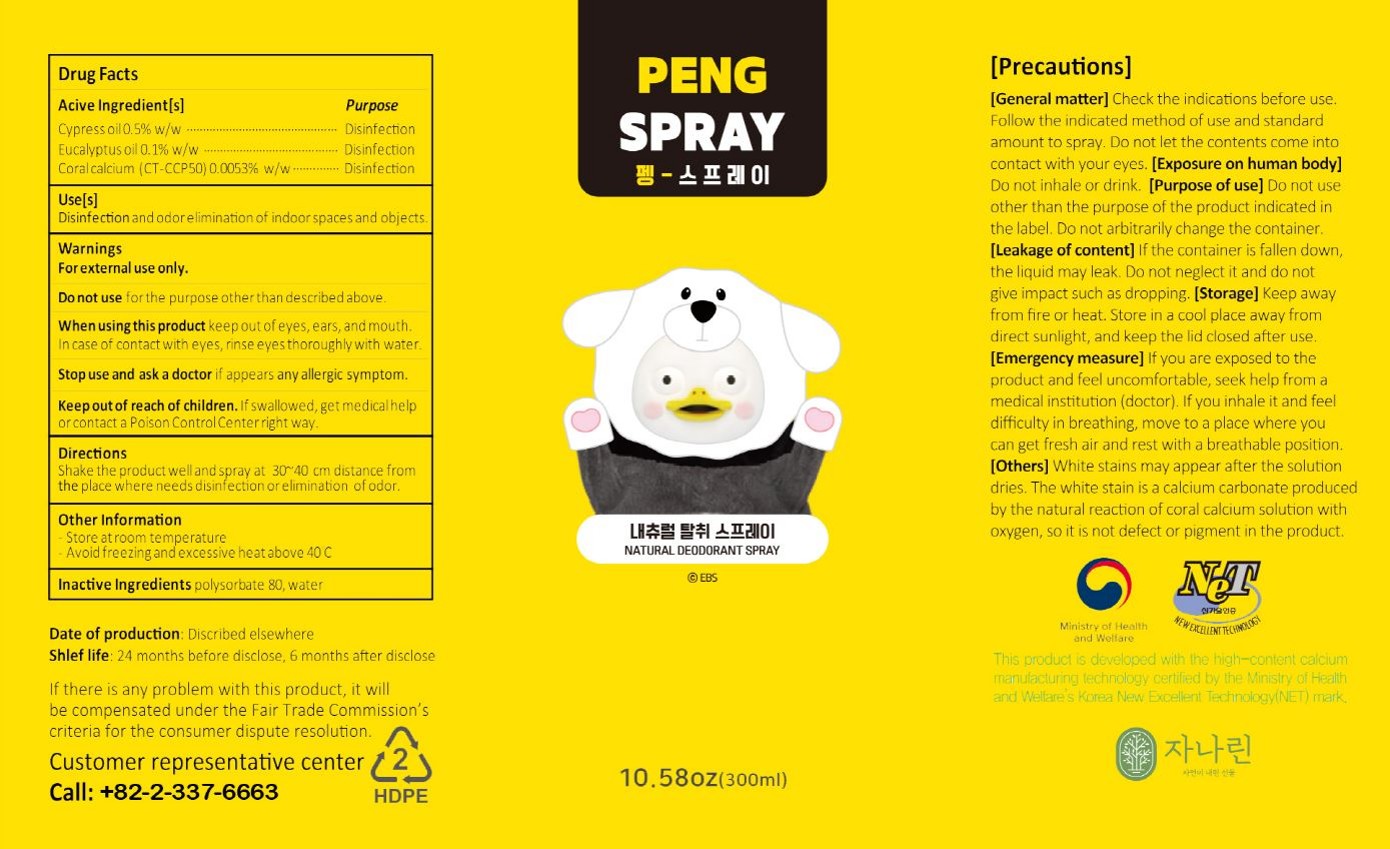 DRUG LABEL: PENGSPRAY
NDC: 83635-301 | Form: SPRAY
Manufacturer: CA GLOBAL
Category: otc | Type: HUMAN OTC DRUG LABEL
Date: 20230724

ACTIVE INGREDIENTS: EUCALYPTUS OIL 0.1 g/100 mL; CUPRESSUS SEMPERVIRENS LEAF OIL 0.5 g/100 mL; OYSTER SHELL CALCIUM CARBONATE, CRUDE 0.0053 g/100 mL
INACTIVE INGREDIENTS: POLYSORBATE 80; WATER

83635-301 PENG SPRAY

Active Ingredients

Cypress oil, Eucalyptus oil, Coral calcium (CT-CCP50)

Purposes

Cypress oil0.5%w/w................................................... Disinfection

Eucalyptus oil 0.1% w/w............................................. Disinfection

Coral calcium (CT-CCP50) 0.0053% w/w .................. Disinfection

Uses

Disinfection and odor elimination of indoor spaces and objects.

Warnings

Do not use for the purpose other than described above.

Warnings

Keep out of reach of children. If swallowed, get medical help or contact a Poison Control Center right way.

Warnings

Stop use and ask a doctor r appears any allergic symptom.

Warnings

When using this product keep out of eyes, ears, and mouth.

Warnings

For external use only.

Directions

Shake the product well and spray at 30~40 cm distance from the place where needs disinfection or elimination of odor.

Inactive Ingredients

polysorbate 80, water